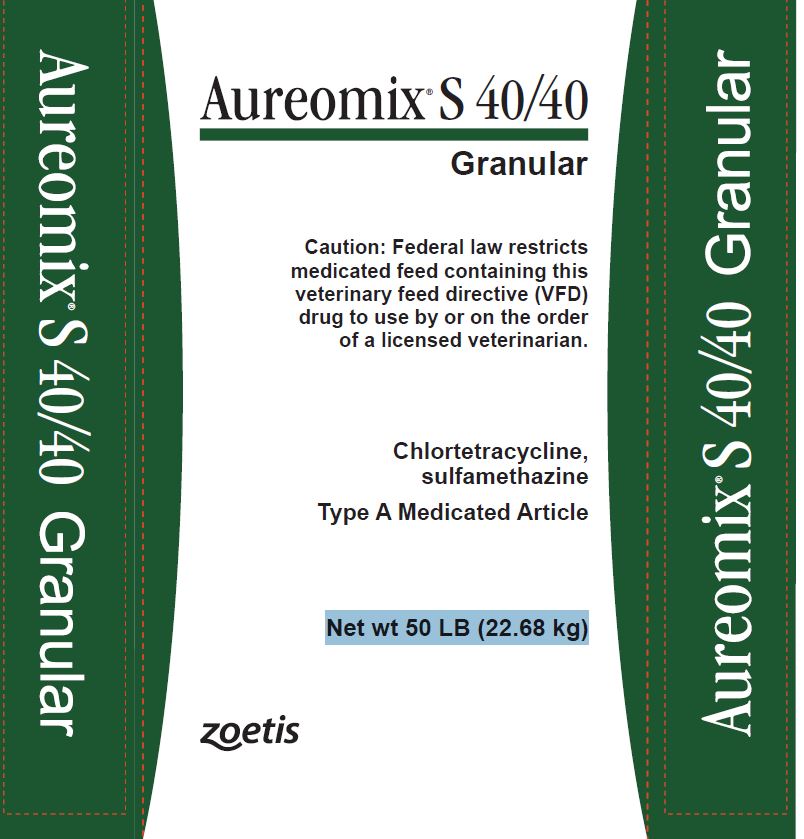 DRUG LABEL: AUREOMIX S 40/40 GRANULAR
NDC: 54771-1018 | Form: GRANULE
Manufacturer: Zoetis Inc.
Category: animal | Type: VFD TYPE A MEDICATED ARTICLE ANIMAL DRUG LABEL
Date: 20170511

ACTIVE INGREDIENTS: CHLORTETRACYCLINE 40 g/.45 kg; SULFAMETHAZINE 40 g/.45 kg
INACTIVE INGREDIENTS: CALCIUM SULFATE

Aureomix S 40/40 Granular

Description

Chlortetracycline, sulfamethazine

Type A Medicated Article

Active Drug Ingredients

Chlortetracycline calcium complex equivalent to chlortetracycline HCI . . . 40 g/lb

Sulfamethazine . . . . . . . . . . . . . . . . . . . . . . . . . . . . . . . . . . . . . . . . 8.8% (40 g/lb)

Ingredients

Calcium sulfate and dried Streptomyces aureofaciens fermentation product.

Indications

For use in the manufacture of swine feeds

For reduction of the incidence of cervical abscesses; treatment of bacterial swine enteritis (salmonellosis or necrotic enteritis caused by Salmonella choleraesuis and vibrionic dysentery); prevention of these diseases during times of stress; and maintenance of weight gains in the presence of atrophic rhinitis.

Mixing Directions

Use 2.5 lb Aureomix® S 40/40 Granular per 1 ton (907.2 kg) of final feed. Make a preblend of 2.5 lb of Aureomix® S 40/40 Granular with part (15-20 lb) of the feed ingredients. Mix thoroughly with the remainder of the ingredients to give a final concentration of 100 g chlortetracycline and 100 g sulfamethazine per ton of feed.

Warning

Withdraw 15 days prior to slaughter

Storage

Store below 25°C (77°F), excursions permitted to 37°C (99°F).

Restricted Drug (California) - use only as directed. Not for human use.

NADA #35-688, Approved by FDA

Distributed by:

Zoetis Inc.

Kalamazoo, MI 49007

Net wt 50 LB (22.68 kg)

10006101

PRINCIPAL DISPLAY PANEL

Aureomix S 40/40 Granular

Caution: Federal law restricts medicated feed containing this veterinary feed directive (VFD) drug to use by or on the order of a licensed veterinarian

Chlortetracycline,

sulfamethazine

Type A Medicated Article

Net wt 50 LB (22.68 kg)

Zoetis